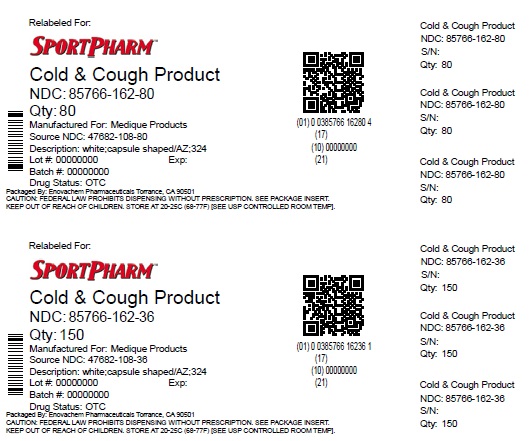 DRUG LABEL: Medique Cold Cough Product
NDC: 85766-162 | Form: TABLET, FILM COATED
Manufacturer: Sportpharm LLC
Category: otc | Type: HUMAN OTC DRUG LABEL
Date: 20260209

ACTIVE INGREDIENTS: DEXTROMETHORPHAN HYDROBROMIDE 10 mg/1 1; ACETAMINOPHEN 325 mg/1 1; PHENYLEPHRINE HYDROCHLORIDE 5 mg/1 1
INACTIVE INGREDIENTS: STARCH, CORN; CROSPOVIDONE; HYPROMELLOSE, UNSPECIFIED; MAGNESIUM STEARATE; STEARIC ACID; TITANIUM DIOXIDE; POLYETHYLENE GLYCOL, UNSPECIFIED; CROSCARMELLOSE SODIUM; MICROCRYSTALLINE CELLULOSE; POVIDONE; SILICON DIOXIDE

Medique Cold & Cough

Drug Facts

Active ingredients (in each caplet)

Acetaminophen 325 mg

Dextromethorphan HBr 10 mg

Phenylephrine Hydrochloride 5 mg

Purpose

Pain reliever/fever reducer

Cough suppressant

Nasal decongestant

Uses

temporarily relieves these common cold/flu symptoms:
■ minor aches and pains
■ headache
■ sore throat
■ nasal congestion
■ cough
■ sinus congestion and pressure
■ helps loosen phlegm (mucus) and thin bronchial secretions to make coughs more productive
temporarily reduces fever.

Warnings

Liver warning:This product contains acetaminophen. Severe liver damage may occur if you take:

■ more than 12 caplets in 24 hours, which is the maximum daily amount

■ with other drugs containing acetaminophen

■ 3 or more alcoholic drinks every day while using this product

Allergy alert:acetaminophen may cause a severe skin reactions. Symptoms may include:

■ skin reddening

■ blisters

■ rash

If a skin reaction occurs, stop use and seek medical help immediately.

Sore throat warning:

If sore throat is severe, persists for more than 2 days, is accompanied or followed by fever, headache, rash, nausea or vomiting, consult a doctor promptly.

Do not use
■ with any other drug containing acetaminophen (prescription or nonprescription). If you are not sure whether a drug contains acetaminophen, ask a doctor or pharmacist.
■ if you are now taking a prescription monoamine oxidase inhibitor (MAOI) (certain drugs for depression, psychiatric or emotional conditions, or Parkinson's disease), or for 2 weeks after stopping the MAOI drugs. If you do not know if your prescription drug contains an MAOI, ask a doctor or pharmacist.

Ask a doctor before use if you have

■ liver disease

■ heart disease

■ high blood pressure

■ thyroid disease

■ diabetes

■ trouble urinating due to an enlarged prostate gland

■ persistent or chronic cough such as occurs with smoking, asthma, or emphysema

■ cough that occurs with too much phlegm (mucus)

Ask a doctor or pharmacist before use if you aretaking the blood thinning drug warfarin.

When using this product do not exceed recommended dosage.

Stop use and ask a doctor if

■ nervousness, dizziness, or sleeplessness occur

■ pain gets worse or lasts for more than 7 days

■ fever gets worse or lasts more than 3 days

■ redness or swelling is present

■ new symptoms occur

■ cough comes back or occurs with rash or headache that lasts

These could be signs of a serious condition.

PREGNANCY OR BREAST FEEDING

If pregnant or breast-feeding,ask a health professional before use.

Keep out of reach of children.In case of accidental overdose, contact a doctor or Poison Control Center (1-800-222-1222) immediately. Taking more than the recommended dose (overdose) may cause liver damage. Quick medical attention is critical for adults as well as for children even if you do not notice any signs or symptoms.

Directions

do not take more than directed (see Warnings)

Adults and children: (12 years and over)

■ take 2 caplets every 4 hours

■ do not take more than 12 caplets in 24 hours

Children under 12 years:do not use this adult product in children under 12 years of age. This will provide more
than the recommended dose (overdose) and may cause liver damage.

Other information

■ store at 25°C (77°F); excursions permitted between 15°-30°C (59°-86°F)

■ tamper evident sealed packets

■ do not use any opened or torn packets

Inactive ingredients

colloidal silicon dioxide, corn starch, croscarmellose sodium, crospovidone, hydroxypropyl methylcellulose, magnesium stearate, microcrystalline cellulose, polyethylene glycol, povidone, pregelatinized starch, silicon dioxide, stearic acid, titanium dioxide

Questions or comments?1-800-634-7680